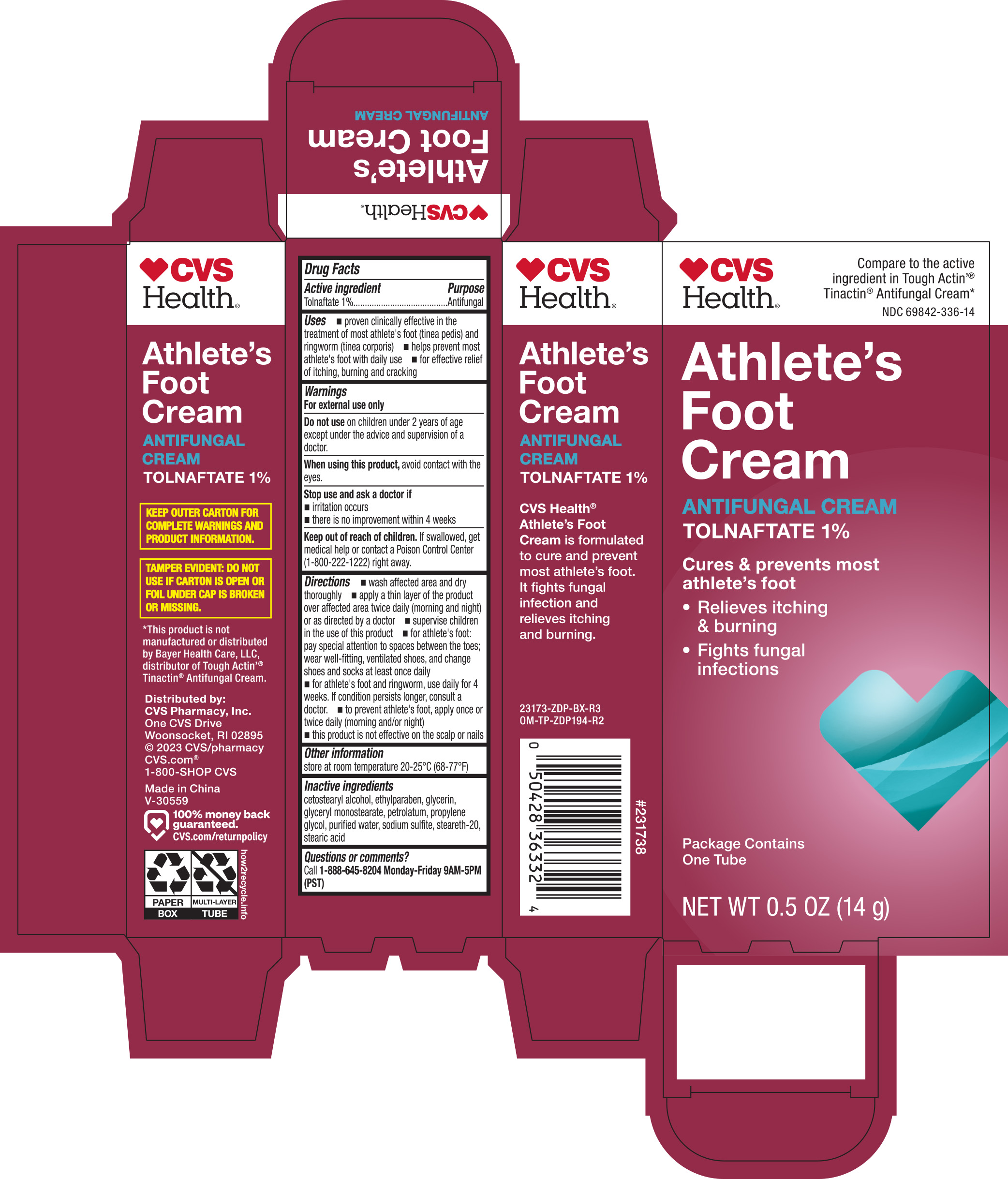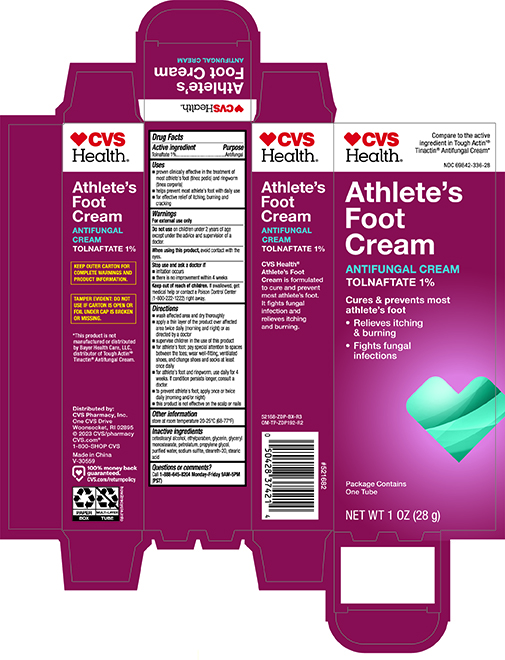 DRUG LABEL: CVS Health Athletes Foot
NDC: 69842-336 | Form: CREAM
Manufacturer: CVS Pharmacy, Inc.
Category: otc | Type: HUMAN OTC DRUG LABEL
Date: 20251029

ACTIVE INGREDIENTS: TOLNAFTATE 10 mg/1 g
INACTIVE INGREDIENTS: STEARETH-20; GLYCERYL MONOSTEARATE; PETROLATUM; ETHYLPARABEN; PROPYLENE GLYCOL; WATER; SODIUM SULFITE; STEARIC ACID; CETOSTEARYL ALCOHOL; GLYCERIN

CVS Athlete's Foot Cream 0.5 23173 ZDP

Active ingredient Purpose

Tolnaftate 1%..................................................................Antifungal

Uses

- proven clinically effective in the treatment of most athlete's foot (tinea pedis) and ringworm (tinea corporis)
- helps prevent most athlete's foot with daily use
- for effective relief of itching, burning and cracking

Warnings

For external use only

Do not use on children under 2 years of age except under the advice and supervision of a doctor

When using this product, avoid contact with the eyes

Stop use and ask a doctor if

- irritation occurs
- there is no improvement within 4 weeks

Keep out of reach of children. If swallowed, get medical help or contact a Poison Control Center (1-800-222-1222) right away

Directions

- wash affected area and dry thoroughly
- apply a thin layer of the product over affected area twice daily (morning and night) or as directed by a doctor
- supervise children in the use of this product
- for athlete's foot: pay special attention to spaces between the toes; wear well-fitting, ventilated shoes, and change shoes and socks at least once daily
- for athlete's foot and ringworm, use daily for 4 weeks. If condition persists longer, consult a doctor
- to prevent athlete's foot, apply once or twice daily (morning and/or night)
- this product is not effective on the scalp or nails

Other information

- store at room temperature 20-25°C (68-77°F)

Inactive ingredients

cetostearyl alcohol, ethylparaben, glycerin, glyceryl monostearate, petrolatum, propylene glycol, purified water, sodium sulfite, steareth-20, stearic acid

DOSAGE AND ADMINISTRATION

Distributed by:

CVS Pharmacy, Inc.

One CVS Drive

Woonsocket, RI 02895